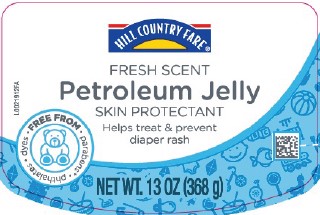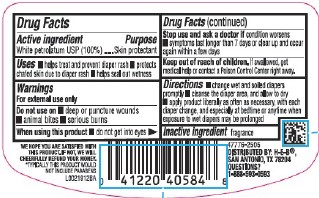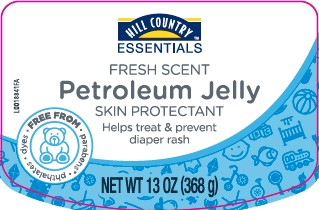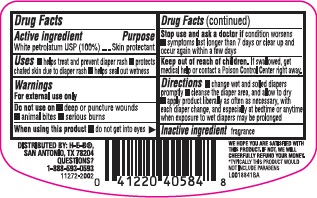 DRUG LABEL: Petroleum
NDC: 37808-519 | Form: JELLY
Manufacturer: H E B
Category: otc | Type: HUMAN OTC DRUG LABEL
Date: 20260224

ACTIVE INGREDIENTS: PETROLATUM 100 g/100 g

HEB Hill Country_HCF 519.001/519AE
Baby Petroleum Jelly

Active ingredient

White Petrolatum USP (100%)

Purpose

Skin protectant

Uses

- helps treat and prevent diaper rash
- protects chafed skin due to diaper rash
- helps seal out wetness

Warnings

For external use only

Do not use on

- deep or puncture wounds
- animal bites
- serious burns

When using this product

- do not get into eyes

Stop use and ask a doctor

- condition worsens
- symptoms longer than 7 days or clear up and occur again within a few days

Keep out of reach of children.

If swallowed, get medical help or contact a Poison Control Center right away.

Directions

- change wet and soiled diapers promptly
- cleanse the diaper area, and allow to dry
- apply product liberally as often as necessary, with each diaper change, and especially at bedtime or anytime when exposure to wet diapers may be prolonged

Inactive ingredient

fragrance

Disclaimer

WE HOPE YOU ARE SATISFIED WITH THIS PRODUCT. IF NOT, WE WILL CHEERFULLY REFUND YOUR MONEY.

*TYPICALLY THIS PRODUCT WOULD NOT INCLUDE PARABENS

Adverse Reactions

DISTRIBUTED BY: H-E-B®

SAN ANTONIO, TX 78204

QUESTIONS?

1-888-593-0593

PRINCIPAL DISPLAY PANEL

HILL COUNTRY FARE®

FRESH SCENT

Petroleum Jelly

SKIN PROTECTANT

Helps treat & prevent diaper rash

FREE FROM - parabens* • phthalates • dyes

NET WT. 13 OZ (368 g)

principal display panel

Hill Country ™

Essentials

Fresh Scent

Petroleum Jelly

Skin Protectant

Helps treat & prevent diaper rash

FREE FROM

parabens
phthalates
dyes

NET WT 13 OZ (368 g)